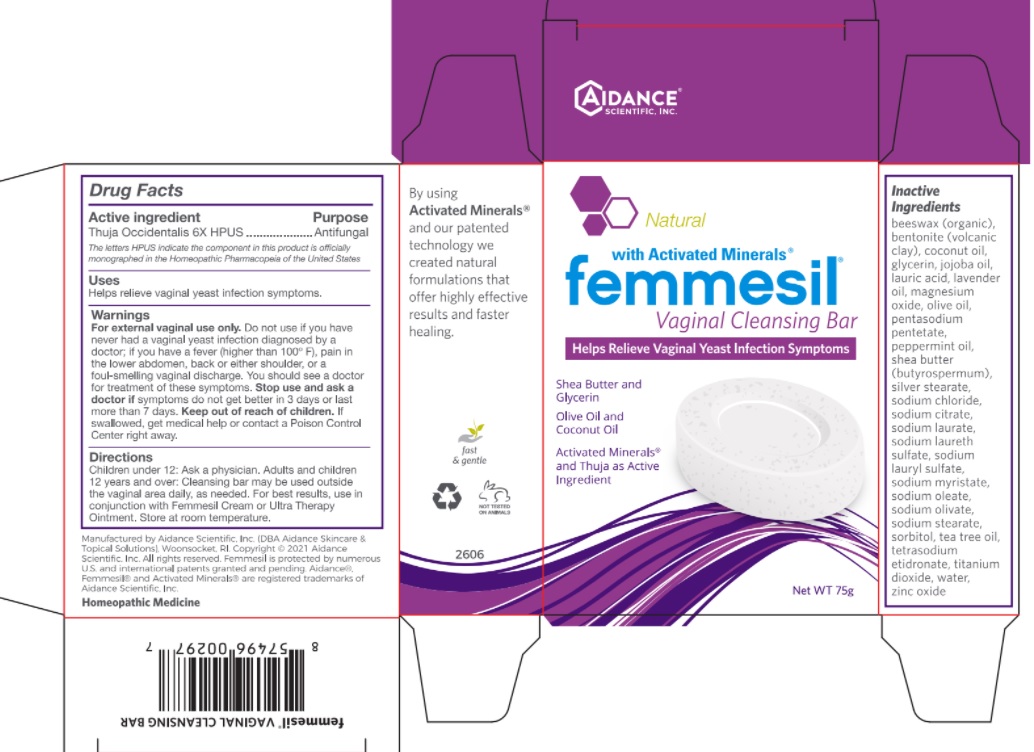 DRUG LABEL: Femmesil Cleansing Bar
NDC: 24909-211 | Form: SOAP
Manufacturer: Aidance Skincare & Topical Solutions, LLC
Category: homeopathic | Type: HUMAN OTC DRUG LABEL
Date: 20220525

ACTIVE INGREDIENTS: THUJA OCCIDENTALIS LEAF 6 [hp_X]/1 g
INACTIVE INGREDIENTS: YELLOW WAX; BENTONITE; COCONUT OIL; GLYCERIN; JOJOBA OIL; LAURIC ACID; LAVENDER OIL; MAGNESIUM OXIDE; OLIVE OIL; PENTASODIUM PENTETATE; PEPPERMINT OIL; SHEA BUTTER; SODIUM CHLORIDE; SODIUM CITRATE; SODIUM LAURATE; SODIUM LAURETH SULFATE; SODIUM LAURYL SULFATE; SODIUM MYRISTATE; SODIUM OLEATE; SODIUM STEARATE; SORBITOL; TEA TREE OIL; ETIDRONATE TETRASODIUM; TITANIUM DIOXIDE; WATER; ZINC OXIDE; SILVER OXIDE; STEARIC ACID; SODIUM OLIVATE

Drug Facts

Active Ingredient

Thuja Occidentalis 6X HPUS

Purpose

Antifungal

The letters HPUS indicate the component in this product is officially monographed in the Homeopathic Pharmacopeia of the United States

Uses

Helps relieve vaginal yeast infection symptoms.

Warnings

For external vaginal use only. Do not use if you have never had a vaginal yeast infection diagnosed by a doctor; if you have a fever (higher than 100° F), pain in the lower abdomen, back, or either shoulder, or a foul-smelling vaginal discharge. You should see a doctor for treatment of these symptoms.

Stop use and ask a doctor if symptoms do not get better in 3 days or last more than 7 days.

Keep out of reach of children.

If swallowed, get medical help or contact a Poison Control Center right away.

Directions

Children under 12: Ask a physician. Adults and children 12 years and over: Cleansing bar may be used outside the vaginal area daily, as needed. For best results, use in conjunction with Femmesil Cream or Ultra Therapy Ointment. Store at room temperature.

Inactive Ingredients

beeswax (organic), bentonite (volcanic clay), coconut oil, glycerin, jojoba oil, lauric acid, lavender oil, magnesium oxide, olive oil, pentasodium pentetate, peppermint oil, shea butter (butyrospermum), silver stearate, sodium chloride, sodium citrate, sodium laurate, sodium laureth sulfate, sodium lauryl sulfate, sodium myristate, sodium oleate, sodium olivate, sodium stearate, sorbitol, tea tree oil, tetrasodium etidronate, titanium dioxide, water, zinc oxide

Questions?

401-432-7750 or www.aidance.com